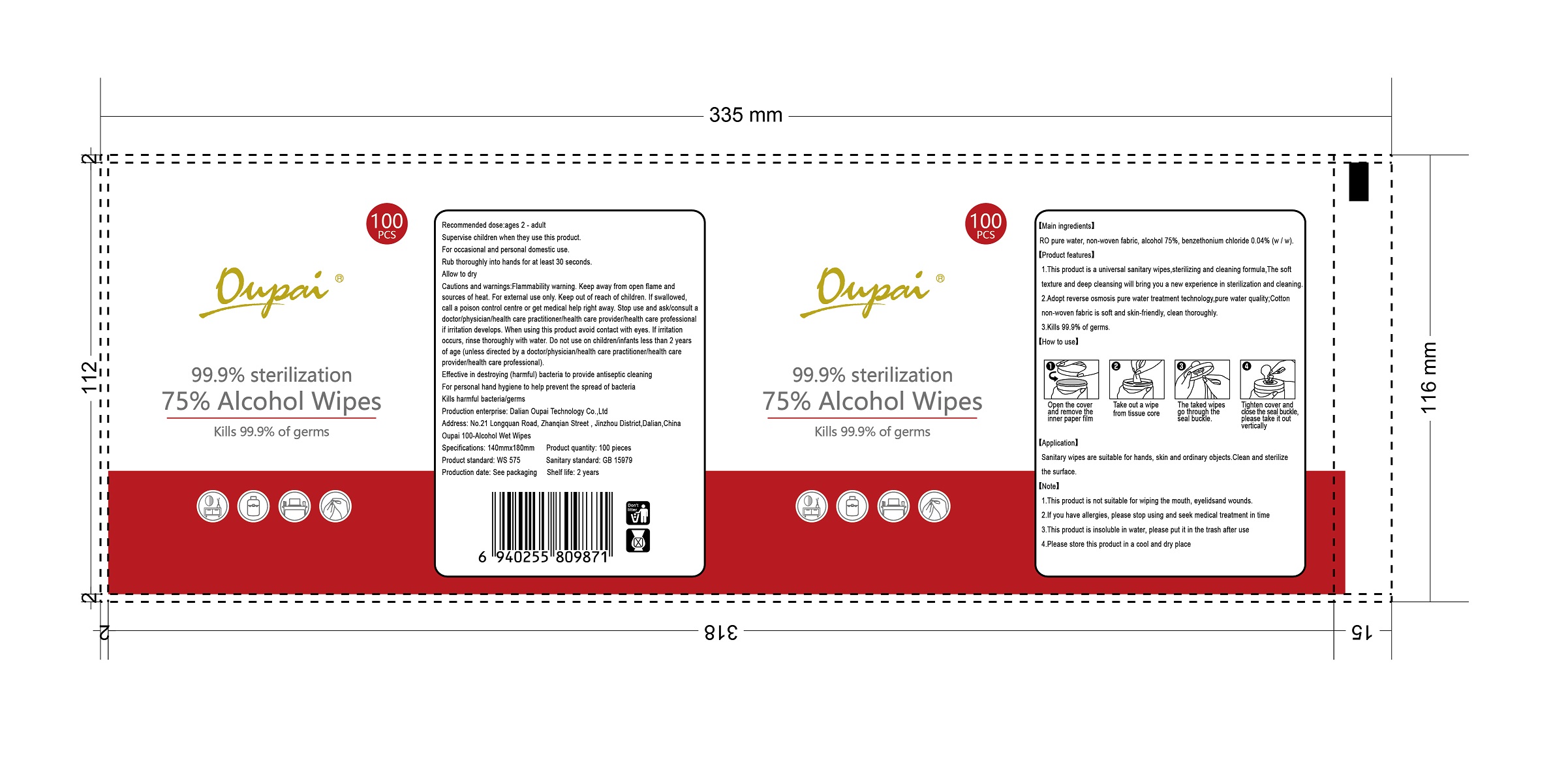 DRUG LABEL: oupai Alcohol wipes
NDC: 78055-005 | Form: CLOTH
Manufacturer: Dalian Oupai Technology Co.,Ltd
Category: otc | Type: HUMAN OTC DRUG LABEL
Date: 20200705

ACTIVE INGREDIENTS: ALCOHOL 0.75 1/1 1
INACTIVE INGREDIENTS: BENZETHONIUM CHLORIDE; WATER

Main ingredient

RO pure water, non-woven fabric, alcohol 75%, benzethonium chloride 0.04% (w / w).

application

sanitary wipe are suitable for hands,skin and ordinary objects,Clean and sterilize the surface

product features

1.This product is a universal sanitary wipes,sterilizing and cleaning formula,The soft

texture and deep cleansing will bring you a new experience in sterilization and cleaning.

2.Adopt reverse osmosis pure water treatment technology,pure water quality;Cotton

non-woven fabric is soft and skin-friendly, clean thoroughly.

3.kills 99.9% of germs

how to use

Open the cover and remove the inner paper film
Take out a wipe from tissue core
The taked wipes go through the seal buckle
Tighten cover and close the seal buckle.please take it out vertically

do not use on children/infants less than 2 years of age(unless directed by doctor/physician/health care practitioner/health care provider/health care professional)

caution and warning

flammability warning.keep away from open flame and source of heat. for external use only.keep out of reach of children. if sawllowed, call a poison contril centre or get medical help right away.stop use and ask concult a doctor physician/health care practitioner/health care provider/health care professional if irritation develops.when using this product avoid contact with eyes. if irritation occurs,rinse thoroughly with water, do not use on children/infants less than 2yeas of age(unless directed by a doctor/physician/health care practitioner/health care provider/health care professional)

Keep out of reach of children.